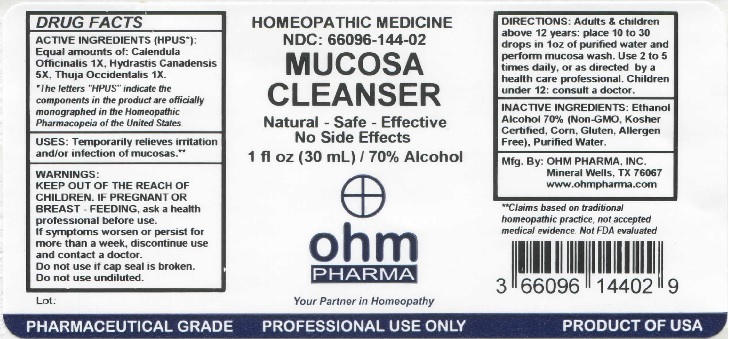 DRUG LABEL: OHM Mucosa Cleanser
NDC: 66096-144 | Form: LIQUID
Manufacturer: OHM PHARMA INC.
Category: homeopathic | Type: HUMAN OTC DRUG LABEL
Date: 20211229

ACTIVE INGREDIENTS: CALENDULA OFFICINALIS FLOWERING TOP 1 [hp_X]/30 mL; GOLDENSEAL 5 [hp_X]/30 mL; THUJA OCCIDENTALIS LEAFY TWIG 1 [hp_X]/30 mL
INACTIVE INGREDIENTS: ALCOHOL; WATER

OHM Mucosa Cleanser

ACTIVE INGREDIENT

ACTIVE INGREDIENTS (HPUS*): Equal amounts of: Calendula Officinalis 1X, Hydrastis Canadensis 5X, Thuja Occidentalis 1X.

*The letters "HPUS" indicate the components in the product are officially monographed in the Homeopathic Pharmacopeia of the United States.

INDICATIONS AND USAGE

Temporarily relieves irritation and/or infection of mucosas.**

**Claims based on traditional homeopathic practice, not accepted medical evidence. Not FDA evaluated.

WARNINGS

WARNINGS: IF PREGNANT OR BREAST-FEEDING, ask a health professional before use. If symptoms worsen or persist for more than a week, discontinue use and contact a doctor.

- KEEP OUT OF REACH OF CHILDREN.

DOSAGE AND ADMINISTRATION

DIRECTIONS: Adults & children above 12 years: place 10 to 30 drops in 1oz of purified water and perform mucosa wash. Use 2 to 5 times daily, or as directed by a health care professional. Children under 12: consult a doctor.

Do not use if cap seal is broken. Do not use undiluted.

INACTIVE INGREDIENT

INACTIVE INGREDIENTS: Ethanol Alcohol 70% (Non-GMO, Kosher Certified, Corn, Gluten, Allergen Free), Purified Water.

QUESTIONS

Mfg. By: OHM PHARMA, INC. Mineral Wells, TX 76067

www.ohmpharma.com

PACKAGE LABEL

HOMEOPATHIC MEDICINE

NDC: 66096-144-02

MUCOSA CLEANSER

Natural - Safe - Effective

No Side Effects

1 fl oz (30mL) / 70% Alcohol

PURPOSE

Mucus Relief